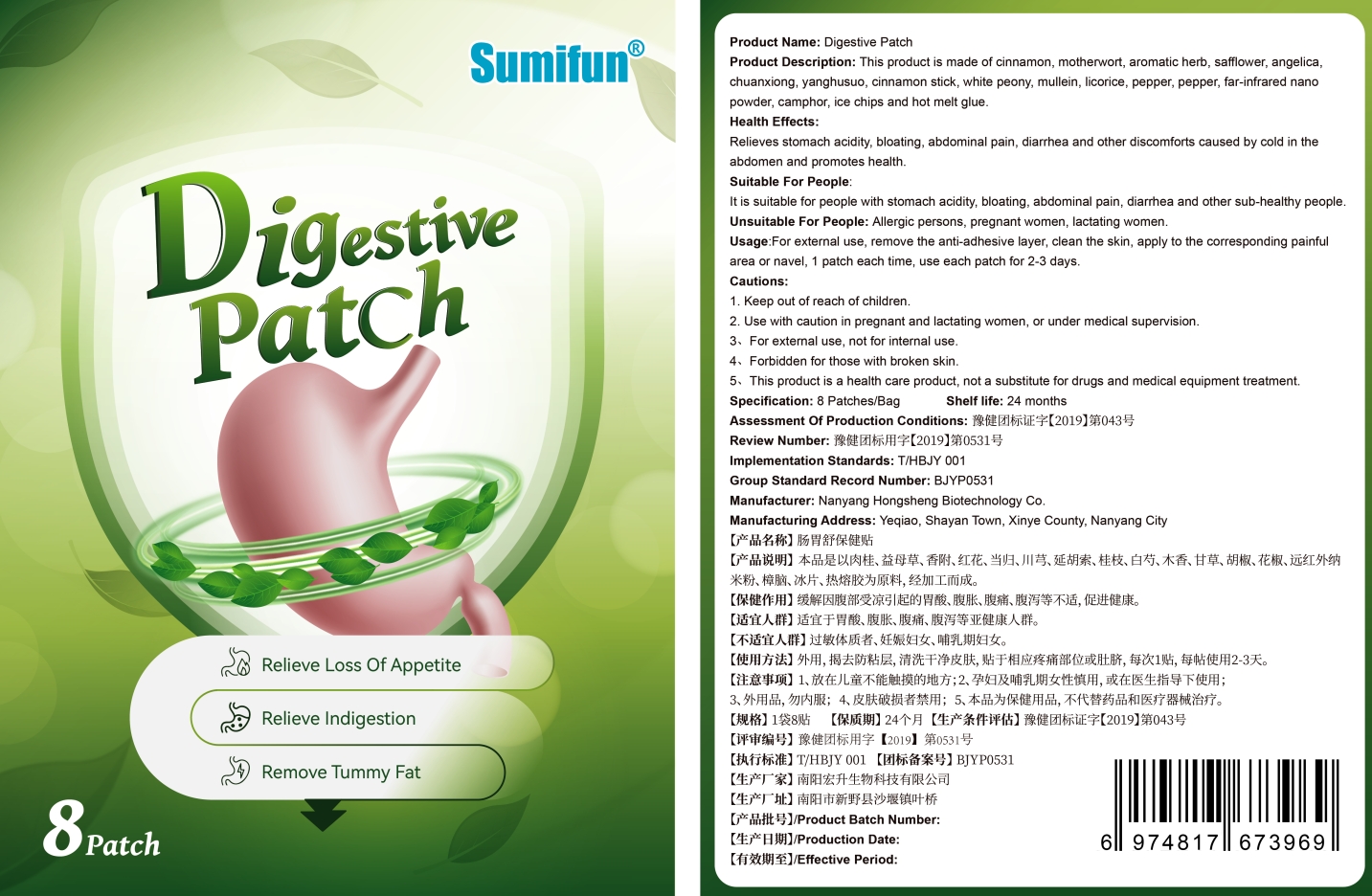 DRUG LABEL: Digestive Patch
NDC: 83675-005 | Form: PATCH
Manufacturer: Guangzhou Hanhai Trading Co., Ltd
Category: otc | Type: HUMAN OTC DRUG LABEL
Date: 20230920

ACTIVE INGREDIENTS: CINNAMON 26 g/100 1
INACTIVE INGREDIENTS: CORYDALIS YANHUSUO TUBER; PAEONIA LACTIFLORA ROOT; LICORICE; MELANOTRANSFERRIN; LEONURUS CARDIACA FLOWERING TOP; ANGELICA SINENSIS ROOT; VERBASCUM PHLOMOIDES FLOWER; BLACK PEPPER; 4-METHYLAMINOREX, CIS-(+/-)-; AMMONIA; BORAGO OFFICINALIS FLOWER; CAMPHOR (NATURAL)

Active Ingredient

Cinnamon 26.0%

Purpose

Help Relieve Loss Of Appetite

Use

Digestive Patch to help relieve loss of appetite

Warnings

For external use only. Do not take it internally.

Keep Out Of Reach Of Children
Pregnant and lactating women use it with caution

Do not use

Product shall not be eat

When Using

Do not stick around eyes and mouth,This product cannot replace drugs or medical equipment for treatment

Stop Use

In case of adverse reactions, please stop using this product.If the symptoms.

Ask Doctor

ask doctor in case of adverse reactions

Keep Oot Of Reach Of Children

Keep Out Of Reach Of Children

Directions

Take one piece of this product when needed, remove the waxpaper,

stick to the desired area and press the surrounding, replace it every 2-3 days .

Children should be used under adult supervision.

Other information

Store the product in a cool, dry and well-ventilated place

Avoid direct sunlight

Inactive ingredients

motherwort,

aromatic herb,

saflower,

angelica chuanxiong,

yanghusuo,

white peony,

mullein,

licorice,

pepper,

camphor,

ice chips ,

hot melt glue